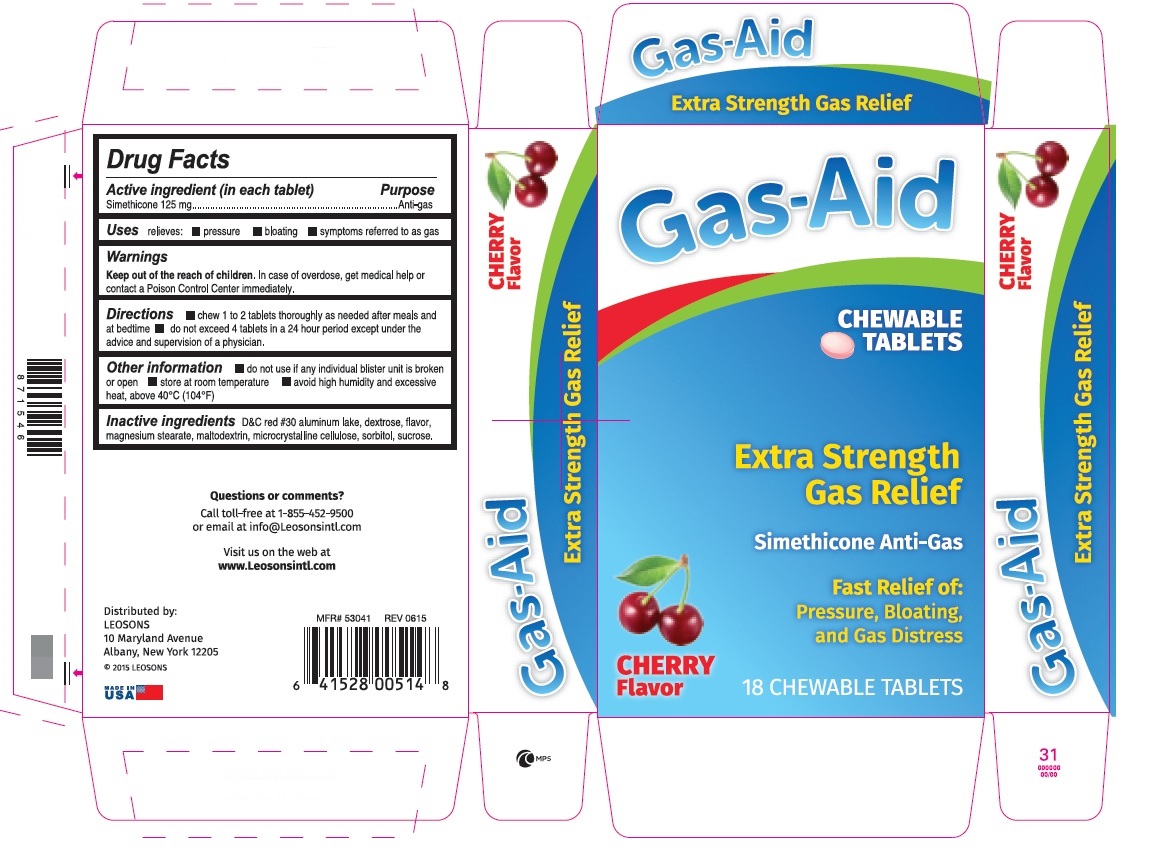 DRUG LABEL: Gas-Aid
NDC: 69626-7197 | Form: TABLET, CHEWABLE
Manufacturer: Leosons Overseas Corp
Category: otc | Type: HUMAN OTC DRUG LABEL
Date: 20241119

ACTIVE INGREDIENTS: DIMETHICONE 125 mg/1 1
INACTIVE INGREDIENTS: D&C RED NO. 30; DEXTROSE; MAGNESIUM STEARATE; MALTODEXTRIN; CELLULOSE, MICROCRYSTALLINE; SORBITOL; SUCROSE

Gas-Aid Extra strength Gas Relief Cherry Flavor

Active ingredient (in each tablet)

Simethicone 125 mg

Purpose

Anti-gas

Uses

relieves:

- pressure
- bloating
- symptoms referred to as gas

Warnings

Keep out of the reach of children. In case of overdose, get medical help or contact a poison control center immediately.

Directions

- chew 1 to 2 tablets thoroughly as needed after meals and at bedtime
- do not exceed 4 tablets in a 24 hour period except under the advice and supervision of a physician

Other information

- do not use if any individual blister unit is broken or open
- store at room temperature
- avoid high humidity and excessive heat, above 40oC (104oF)

Inactive ingredients

D&C red 30 aluminum lake, dextrose, flavor, magnesium stearate, maltodextrin, microcrystalline cellulose, sorbitol, sucrose

Principal Display Panel

Gas-Aid

Extra strength Gas Relief

Simethicone Anti-Gas

Cherry Flavor

Fast Relief of pressure, bloating and gas distress

18 chewable tablets